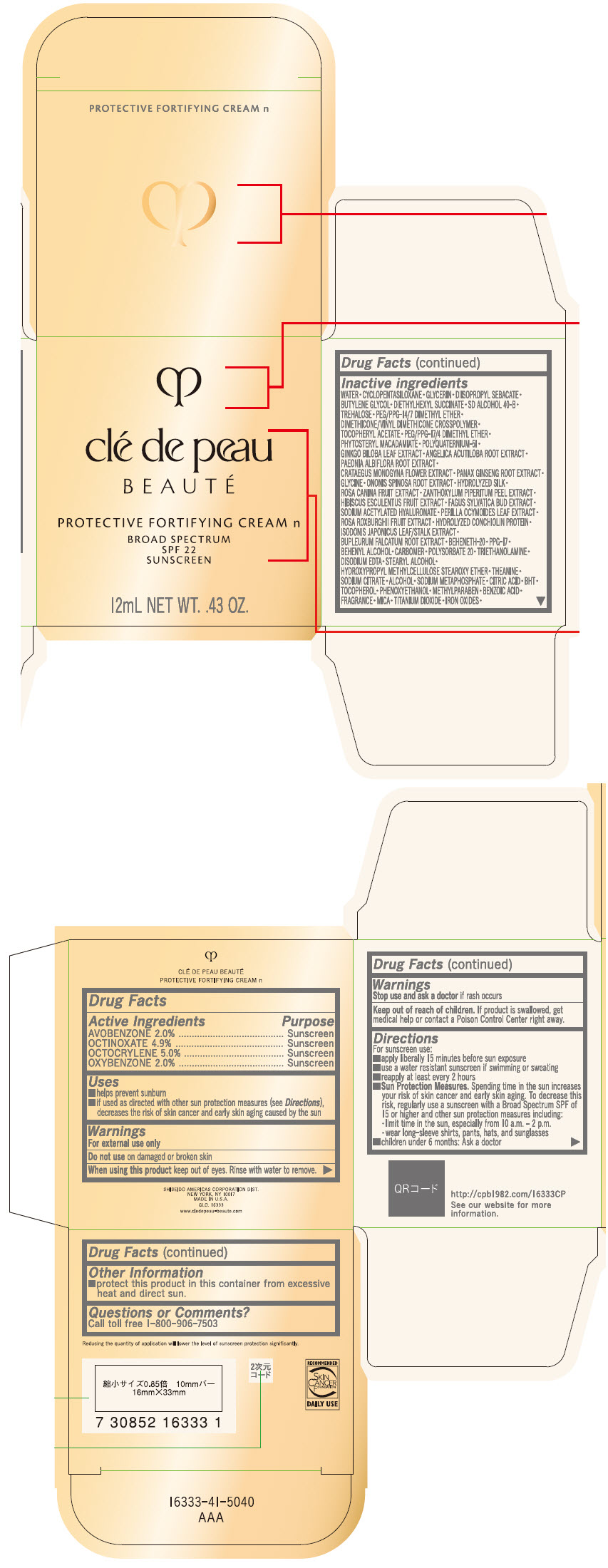 DRUG LABEL: CLE DE PEAU BEAUTE PROTECTIVE FORTIFYING n
NDC: 58411-562 | Form: EMULSION
Manufacturer: SHISEIDO AMERICAS CORPORATION
Category: otc | Type: HUMAN OTC DRUG LABEL
Date: 20260106

ACTIVE INGREDIENTS: AVOBENZONE 0.2472 g/12 mL; OCTINOXATE 0.60564 g/12 mL; OCTOCRYLENE 0.618 g/12 mL; OXYBENZONE 0.2472 g/12 mL
INACTIVE INGREDIENTS: WATER; CYCLOMETHICONE 5; GLYCERIN; DIISOPROPYL SEBACATE; BUTYLENE GLYCOL; DIETHYLHEXYL SUCCINATE; TREHALOSE; PEG/PPG-14/7 DIMETHYL ETHER; DIMETHICONE/VINYL DIMETHICONE CROSSPOLYMER (SOFT PARTICLE); .ALPHA.-TOCOPHEROL ACETATE, DL-; PEG/PPG-17/4 DIMETHYL ETHER; PHYTOSTERYL MACADAMIATE; POLYQUATERNIUM-51 (2-METHACRYLOYLOXYETHYL PHOSPHORYLCHOLINE/N-BUTYL METHACRYLATE; 3:7); GINKGO; ANGELICA ACUTILOBA ROOT; PAEONIA LACTIFLORA ROOT; CRATAEGUS MONOGYNA FLOWER; ASIAN GINSENG; GLYCINE; ONONIS SPINOSA ROOT; ROSA CANINA FRUIT; ZANTHOXYLUM PIPERITUM FRUIT RIND; FAGUS SYLVATICA FLOWER BUD; SODIUM ACETYLATED HYALURONATE; PERILLA FRUTESCENS LEAF; ROSA ROXBURGHII FRUIT; BUPLEURUM FALCATUM ROOT; BEHENETH-20; PPG-17; DOCOSANOL; CARBOMER HOMOPOLYMER, UNSPECIFIED TYPE; POLYSORBATE 20; TROLAMINE; EDETATE DISODIUM; STEARYL ALCOHOL; THEANINE; SODIUM CITRATE, UNSPECIFIED FORM; ALCOHOL; SODIUM POLYMETAPHOSPHATE; CITRIC ACID MONOHYDRATE; BUTYLATED HYDROXYTOLUENE; .ALPHA.-TOCOPHEROL; PHENOXYETHANOL; METHYLPARABEN; BENZOIC ACID; MICA; TITANIUM DIOXIDE; FERRIC OXIDE RED; FERRIC OXIDE YELLOW; FERROSOFERRIC OXIDE

CLÉ DE PEAU BEAUTÉ PROTECTIVE FORTIFYING CREAM n

Drug Facts

ACTIVE INGREDIENT

Active ingredients | Purpose
AVOBENZONE 2.0% | Sunscreen
OCTINOXATE 4.9% | Sunscreen
OCTOCRYLENE 5.0% | Sunscreen
OXYBENZONE 2.0% | Sunscreen

Uses

- helps prevent sunburn
- if used as directed with other sun protection measures (see Directions), decreases the risk of skin cancer and early skin aging caused by the sun

Warnings

For external use only

Do not useon damaged or broken skin

WHEN USING

When using this productkeep out of eyes. Rinse with water to remove.

Stop use and ask a doctorif rash occurs.

Keep out of reach of children.If product is swallowed, get medical help or contact a Poison Control Center right away.

Directions

For sunscreen use:

- apply liberally 15 minutes before sun exposure
- use a water resistant sunscreen if swimming or sweating
- reapply at least every 2 hours
- Sun Protection Measures. Spending time in the sun increases your risk of skin cancer and early skin aging. To decrease this risk, regularly use a sunscreen with a Broad Spectrum SPF of 15 or higher and other un protection measures including:
  - limit time in the sun, especially from 10 a.m. – 2 p.m.
  - wear long-sleeve shirts, pants, hats, and sunglasses
- children under 6 months: Ask a doctor

Inactive Ingredients

WATER•CYCLOPENTASILOXANE•GLYCERIN•DIISOPROPYL SEBACATE•BUTYLENE GLYCOL•DIETHYLHEXYL SUCCINATE•SD ALCOHOL 40-B•TREHALOSE•PEG/PPG-14/7 DIMETHYL ETHER•DIMETHICONE/VINYL DIMETHICONE CROSSPOLYMER•TOCOPHERYL ACETATE•PEG/PPG-17/4 DIMETHYL ETHER•PHYTOSTERYL MACADAMIATE•POLYQUATERNIUM-51•GINKGO BILOBA LEAF EXTRACT•ANGELICA ACUTILOBA ROOT EXTRACT•PAEONIA ALBIFLORA ROOT EXTRACT•CRATAEGUS MONOGYNA FLOWER EXTRACT•PANAX GINSENG ROOT EXTRACT•GLYCINE•ONONIS SPINOSA ROOT EXTRACT•HYDROLYZED SILK•ROSA CANINA FRUIT EXTRACT•ZANTHOXYLUM PIPERITUM PEEL EXTRACT•HIBISCUS ESCULENTUS FRUIT EXTRACT•FAGUS SYLVATICA BUD EXTRACT•SODIUM ACETYLATED HYALURONATE•PERILLA OCYMOIDES LEAF EXTRACT•ROSA ROXBURGHII FRUIT EXTRACT•HYDROLYZED CONCHIOLIN PROTEIN•ISODONIS JAPONICUS LEAF/STALK EXTRACT•BUPLEURUM FALCATUM ROOT EXTRACT•BEHENETH-20•PPG-17•BEHENYL ALCOHOL•CARBOMER•POLYSORBATE 20•TRIETHANOLAMINE•DISODIUM EDTA•STEARYL ALCOHOL•HYDROXYPROPYL METHYLCELLULOSE STEAROXY ETHER•THEANINE•SODIUM CITRATE•ALCOHOL•SODIUM METAPHOSPHATE•CITRIC ACID•BHT•TOCOPHEROL•PHENOXYETHANOL•METHYLPARABEN•BENZOIC ACID•FRAGRANCE•MICA•TITANIUM DIOXIDE•IRON OXIDES•

Other information

- protect this product in this container from excessive heat and direct sun.

Questions or comments?

Call toll free 1-800-906-7503

PRINCIPAL DISPLAY PANEL - 12 mL Bottle Carton

clé de peau
BEAUTÉ

PROTECTIVE FORTIFYING CREAM n
BROAD SPECTRUM
SPF 22
SUNSCREEN

12mL NET WT. .43 OZ.